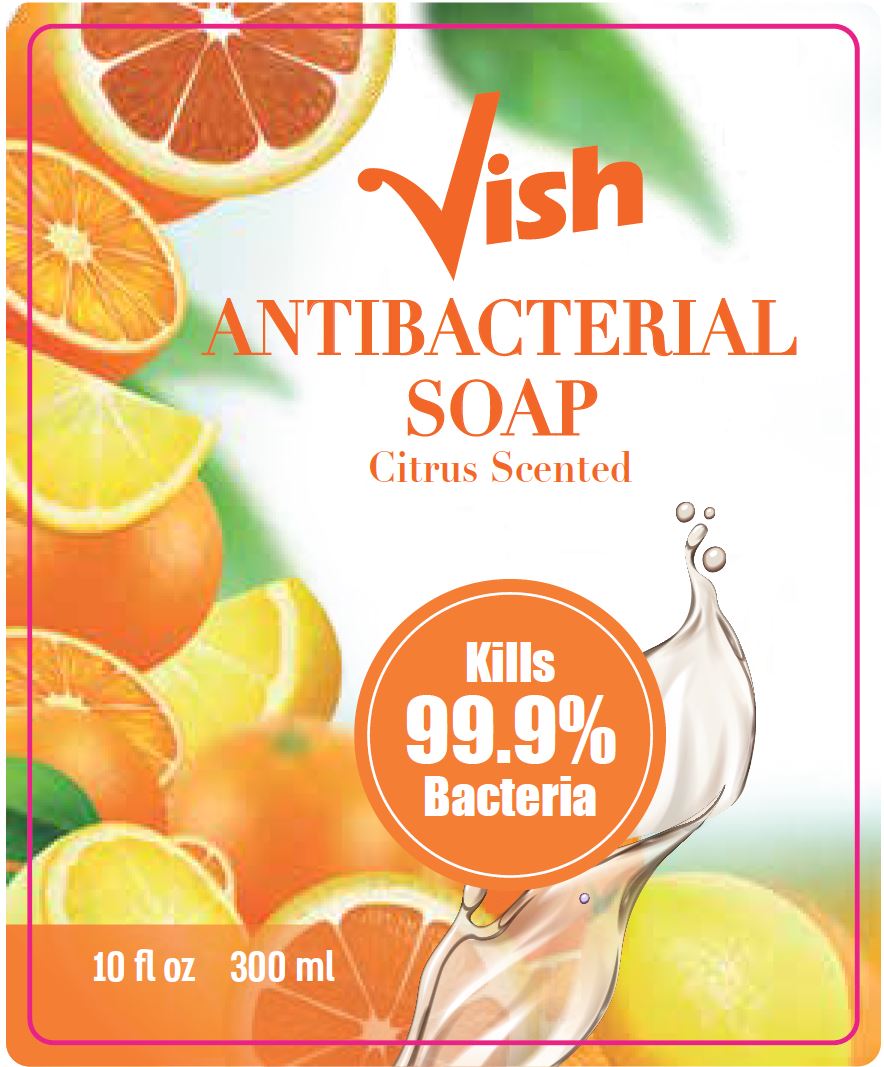 DRUG LABEL: Citrus antibacterial
NDC: 62685-121 | Form: SOAP
Manufacturer: Tropical Degil Cosmetics Industries LTD
Category: otc | Type: HUMAN OTC DRUG LABEL
Date: 20200901

ACTIVE INGREDIENTS: BENZALKONIUM CHLORIDE 0.1755 g/135 g
INACTIVE INGREDIENTS: PEG-120 METHYL GLUCOSE DIOLEATE; SODIUM CHLORIDE; COCO MONOETHANOLAMIDE; CETRIMONIUM CHLORIDE; COCAMIDOPROPYLAMINE OXIDE; METHYLCHLOROISOTHIAZOLINONE; FD&C YELLOW NO. 5; WATER; GLYCERIN; LAURAMINE OXIDE; METHYLISOTHIAZOLINONE; FD&C RED NO. 4

Vish Antibacterial Soap Citrus Scented

Active ingredient

Benzalkonium Chloride 0.13%

Purpose

Antibacterial

Uses

For handwashing to decrease bacteria on the skin.

Warnings

For external use only

When using this product avoid contact with eyes. in case of contact with eyes, rinse eyes thoroughly with water.

Stop use and ask a doctor if irritation or redness develops.

Keep out of reach of children. If swallowed, get medical help or contact a Poison Control Center right away.

Directions

- Pump into hands, wet as needed.
- Lather for at least 15 seconds
- Rinse and dry thoroughly.

Inactive ingredients

Centrimonium Chloride, Cocamide MEA, Cocamidopropylamine Oxide, Fragrance, Glycerin, Lauramine Oxide, Methylchloroisothiazolinone, Methylisothiazolinone, PEG-120 Methyl Glucose Dioleate, Sodium Chloride, Red 4, Yellow 5, Water

PACKAGE LABEL

Vish Antibacterial Soap

Citrus Scented

10 fl oz 300 ml